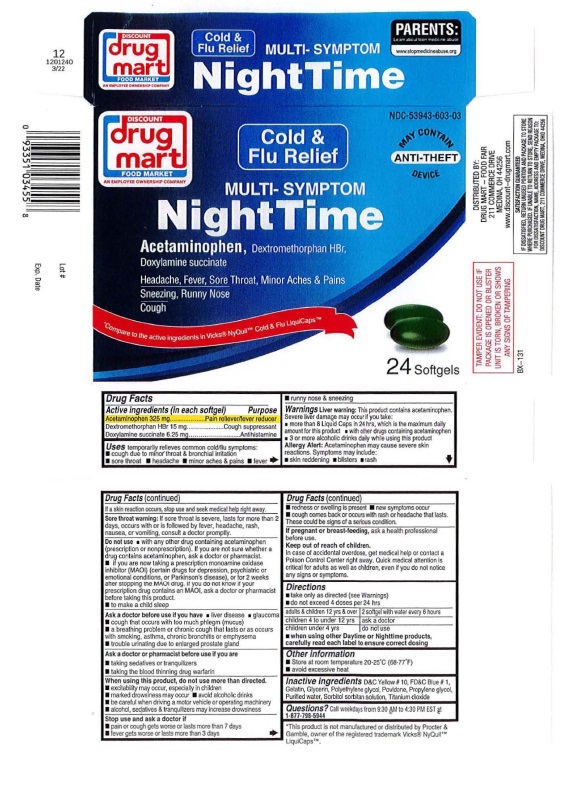 DRUG LABEL: Night Time Multi-Symptom Cold and Flu Relief
NDC: 53943-603 | Form: CAPSULE, LIQUID FILLED
Manufacturer: Discount Drug Mart
Category: otc | Type: HUMAN OTC DRUG LABEL
Date: 20251219

ACTIVE INGREDIENTS: ACETAMINOPHEN 325 mg/1 1; DEXTROMETHORPHAN HYDROBROMIDE 15 mg/1 1; DOXYLAMINE SUCCINATE 6.25 mg/1 1
INACTIVE INGREDIENTS: D&C YELLOW NO. 10; FD&C BLUE NO. 1; GELATIN; GLYCERIN; POLYETHYLENE GLYCOL, UNSPECIFIED; POVIDONE; PROPYLENE GLYCOL; WATER; SORBITOL SOLUTION; TITANIUM DIOXIDE

DISCOUNT drug mart Night Time Multi-Symptom Cold & Flu Relief

Drug Facts

Active Ingredients (In each softgel)

Acetaminophen 325 mg
Dextromethorphan HBr 15 mg
Doxylamine succinate 6.25 mg

Purpose
Acetaminophen Pain reliever/Fever reducer
Dextromethorphan HBr Cough suppressant
Doxylamine succinate Antihistamine

INDICATIONS AND USAGE

UsesTemporarily relieves common cold and flu symptoms:
• cough due to minor throat and bronchial irritation
• sore throat
• minor aches and pain
• fever
• runny nose and sneezing

Warnings
Liver warning:This product contains acetaminophen.
Severe liver damage may occur if you take:
• more than 8 Liquid Caps in 24 hours, which is the maximum daily
amount for this product • with other drugs containing acetaminophen
• 3 or more alcoholic drinks daily while using this product
Allergy alert:Acetaminophen may cause severe skin
reactions. Symptoms may include:
• skin reddening • blisters • rash.
If a skin reaction occurs, stop use and seek medical help right away.
Sore throat warning: If sore throat is severe, lasts for more than
2 days, occurs with or is followed by fever, headache, rash,
nausea or vomiting, consult a doctor promptly.

Do not use• with any other drug containing acetaminophen
(prescription or nonprescription). If you are not sure whether a
drug contains acetaminophen, ask a doctor or pharmacist
• if you are now taking a prescription monoamine oxidase
inhibitor (MAOI) (certain drugs for depression, psychiatric, or
emotional conditions, or Parkinson's disease), or for 2 weeks
after stopping the MAOI drug. If you do not know if your
prescription drug contains an MAOI, ask a doctor or pharmacist
before taking this product.

• to make a child sleep

Ask a doctor before use if you have • liver disease • glaucoma
• cough that occurs with too much phlegm (mucus)
• a breathing problem or chronic cough that lasts or as occurs
with smoking, asthma, chronic bronchitis or emphysema
• trouble urinating due to an enlarged prostate gland

Ask a doctor or pharmacist before use if you are

• taking sedatives or tranquilizers

• taking the blood thinning drug warfarin

When using this product, do not use more than directed.
• excitability may occur, especially in children,
• marked drowsiness may occur
• avoid alcoholic drinks
• be careful when driving a motor vehicle or operating machinery
• alcohol, sedatives, and tranquilizers may increase drowsiness

Stop use and ask a doctor if
• pain or cough gets worse or lasts more than 7 days
• fever gets worse or lasts more than 3 days
• redness or swelling is present • new symptoms occur
• cough comes back or occurs with rash or headache that lasts.
These could be signs of a serious condition.

PREGNANCY OR BREAST FEEDING

If pregnant or breast feeding,ask a health professional before use.

Keep out of reach of children.In case of accidental overdose, get medical help or contact a Poison Control Center right
away. Quick medical attention is critical for adults as well as for children, even if you do not notice any signs or
symptoms.

Directions
• take only as directed (see Warning)
• do not exceed 4 doses per 24 hours

Adults and Children 12 yrs & over | 2 softgels with water every 6 hours
Children 4 to under 12 yrs | ask a doctor
Children under 4 yrs | do not use

• when using other Daytime or Nighttime products,
carefully read each label to ensure correct dosing

Other information

• store at room temperature 20-2S·C (68-77"F)
• avoid excessive heat

INACTIVE INGREDIENT

Inactive ingredientsD&C Yellow # 10, FD&C Blue # 1,
Gelatin, glycerin, Polyethylene glycol, Povidone, Propylene Glycol,
Purified water, Sorbitol sorbitan solution, Titanium dioxide.

QUESTIONS

Questions?Call Weekdays from 9:30 AM to 4:30 PM EST at 1-877-798-5944

Package Labeling: DISCOUNT drug mart Night Time Multi-Symptom Cold & Flu Relief

DISCOUNT NDC-53943-603-03

drug mart

FOOD MARKET

Cold &
Flu Relief

MULTI-SYMPTOM

NIGHT TIME

*Compare to the active ingredients in Vicks®NyQuil™ Cold & Flu LiquiCaps™

24 Softgels

DISTRIBUTED BY:

DRUG MART - FOOD FAIR

211 COMMERCE DRIVE

MEDINA, OH 44256

www.discount-drugmart.com

This product is not manufactured or distributed by Procter
& Gamble, owner of the registered trademark Vicks®
DayOuilTMLiquiCapsTM

TAMPER EVIDENT: DO NOT USE IF

PACKAGE IS OPENED OR BLISTER

UNIT IS TORN, BROKEN OR SHOWS

ANY SIGNS OF TAMPERING

IF DISSATISFIED, RETURN UNUSED PORTION AND PACKAGE TO STORE

WHERE PURCHASED. IF UNABLE TO RETURN TO STORE, SEND REASON

FOR DISSATISFACTION , NAME, ADDRESS AND EMPTY PACKAGE TO:

DISCOUNT DRUG MART, 211 COMMERCE DRIVE MEDINNA, OHIO 44256